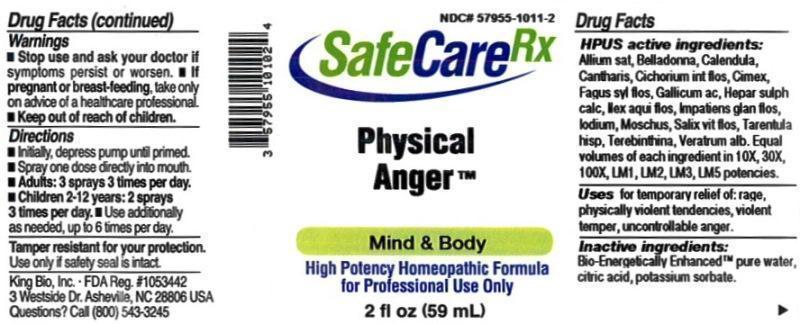 DRUG LABEL: Physical Anger
NDC: 57955-1011 | Form: LIQUID
Manufacturer: King Bio Inc.
Category: homeopathic | Type: HUMAN OTC DRUG LABEL
Date: 20150609

ACTIVE INGREDIENTS: GARLIC 10 [hp_X]/59 mL; ATROPA BELLADONNA 10 [hp_X]/59 mL; CALENDULA OFFICINALIS FLOWERING TOP 10 [hp_X]/59 mL; LYTTA VESICATORIA 10 [hp_X]/59 mL; CICHORIUM INTYBUS FLOWER 10 [hp_X]/59 mL; CIMEX LECTULARIUS 10 [hp_X]/59 mL; FAGUS SYLVATICA FLOWERING TOP 10 [hp_X]/59 mL; GALLIC ACID MONOHYDRATE 10 [hp_X]/59 mL; CALCIUM SULFIDE 10 [hp_X]/59 mL; ILEX AQUIFOLIUM FLOWERING TOP 10 [hp_X]/59 mL; IMPATIENS GLANDULIFERA FLOWER 10 [hp_X]/59 mL; IODINE 10 [hp_X]/59 mL; MOSCHUS MOSCHIFERUS MUSK SAC RESIN 10 [hp_X]/59 mL; SALIX ALBA FLOWERING TOP 10 [hp_X]/59 mL
INACTIVE INGREDIENTS: WATER; ANHYDROUS CITRIC ACID; POTASSIUM SORBATE

Physical Anger™

ACTIVE INGREDIENT

Drug Facts__________________________________________________________________________________________________________

HPUS active ingredients: Allium sativum, Belladonna, Calendula officinalis, Cantharis, Cichorium intybus, flos, Cimex lectularius, Fagus sylvatica, flos, Gallicum acidum, Hepar sulphuris calcareum, Ilex aquifolium, flos, Impatiens glandulifera, flos, Iodium, Moschus, Salix vitellina, flos. Equal volumes of each ingredient in 10X, 30X, 100X, LM1, LM2, LM3, LM5 potencies.

INDICATIONS AND USAGE

Uses for temporary relief of: rage, physically violent tendencies, violent temper, uncontrollable anger.

Inactive Ingredients:

Bio-Energetically Enhanced™ pure water, citric acid and potassium sorbate.

Warnings

- Stop use and ask your doctor if symptoms persist or worsen.
- If pregnant or breast-feeding, take only on advice of a healthcare professional.

- Keep out of reach of children.

Directions

- Initially, depress pump until primed.
- Spray one dose directly into mouth.
- Adults: 3 sprays 3 times per day.
- Children 2-12 years: 2 sprays 3 times per day.
- Use additionally as needed, up to 6 times per day.

OTHER SAFETY INFORMATION

Tamper resistant for your protection. Use only if safety seal is intact.

PURPOSE

Uses for temporary relief of:

- rage
- physically violent tendencies
- violent temper
- uncontrollable anger